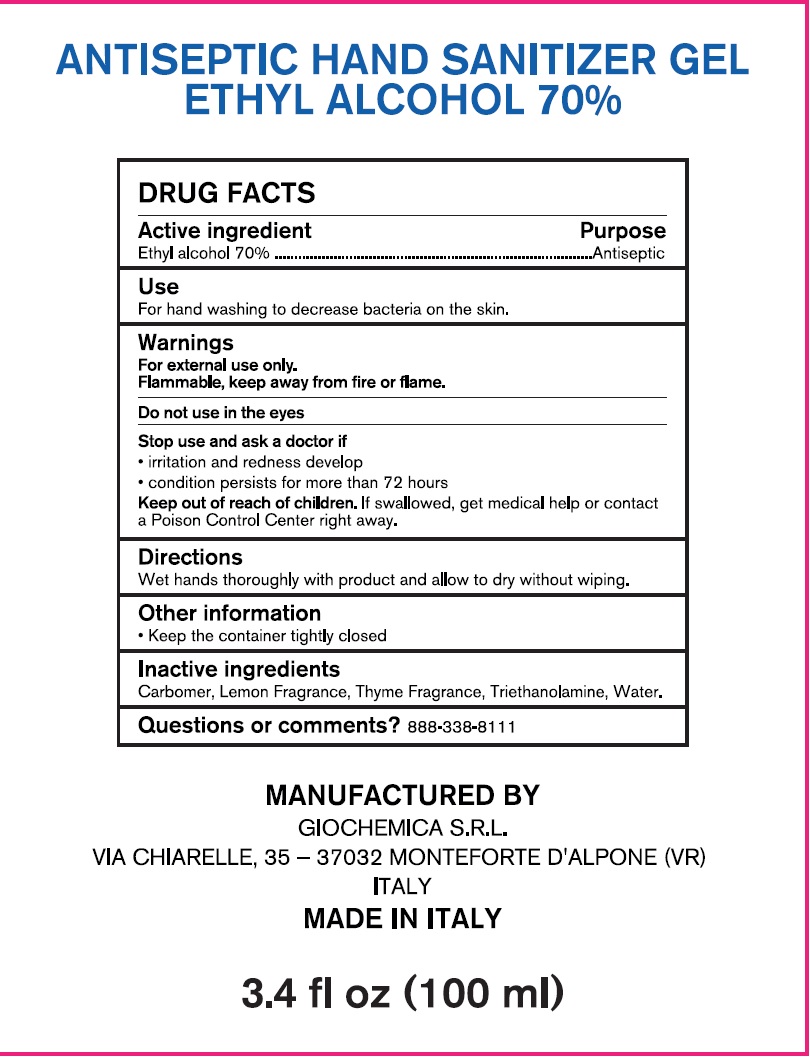 DRUG LABEL: Antiseptic Hand Sanitizer Gel Ethyl Alcohol 70
NDC: 80365-002 | Form: LIQUID
Manufacturer: Adam br srl
Category: otc | Type: HUMAN OTC DRUG LABEL
Date: 20210518

ACTIVE INGREDIENTS: ALCOHOL 70 mL/100 mL
INACTIVE INGREDIENTS: CARBOMER HOMOPOLYMER, UNSPECIFIED TYPE; TROLAMINE; WATER

Antiseptic Hand Sanitizer Gel Ethyl Alcohol 70%

Active ingredient

Ethyl alcohol 70%

Purpose

Antiseptic

Use

For hand washing to decrease bacteria on the skin.

Warnings

For external use only.

Flammable, keep away from fire or flame.

Do not use

in the eyes

Stop use and ask a doctor if

- irritation and redness develop
- condition persists for more than 72 hours

Keep out of reach of children.

If swallowed, get medical help or contact a Poison Control Center right away.

Dierctions

Wet hands thoroughly with product and allow to dry without wiping.

Other information

- Keep the container tightly closed

Inactive ingredients

Carbomer, Lemon Fragrance, Thyme Fragrance, Triethanolamine, Water.

Questions or comments?

888-338-8111